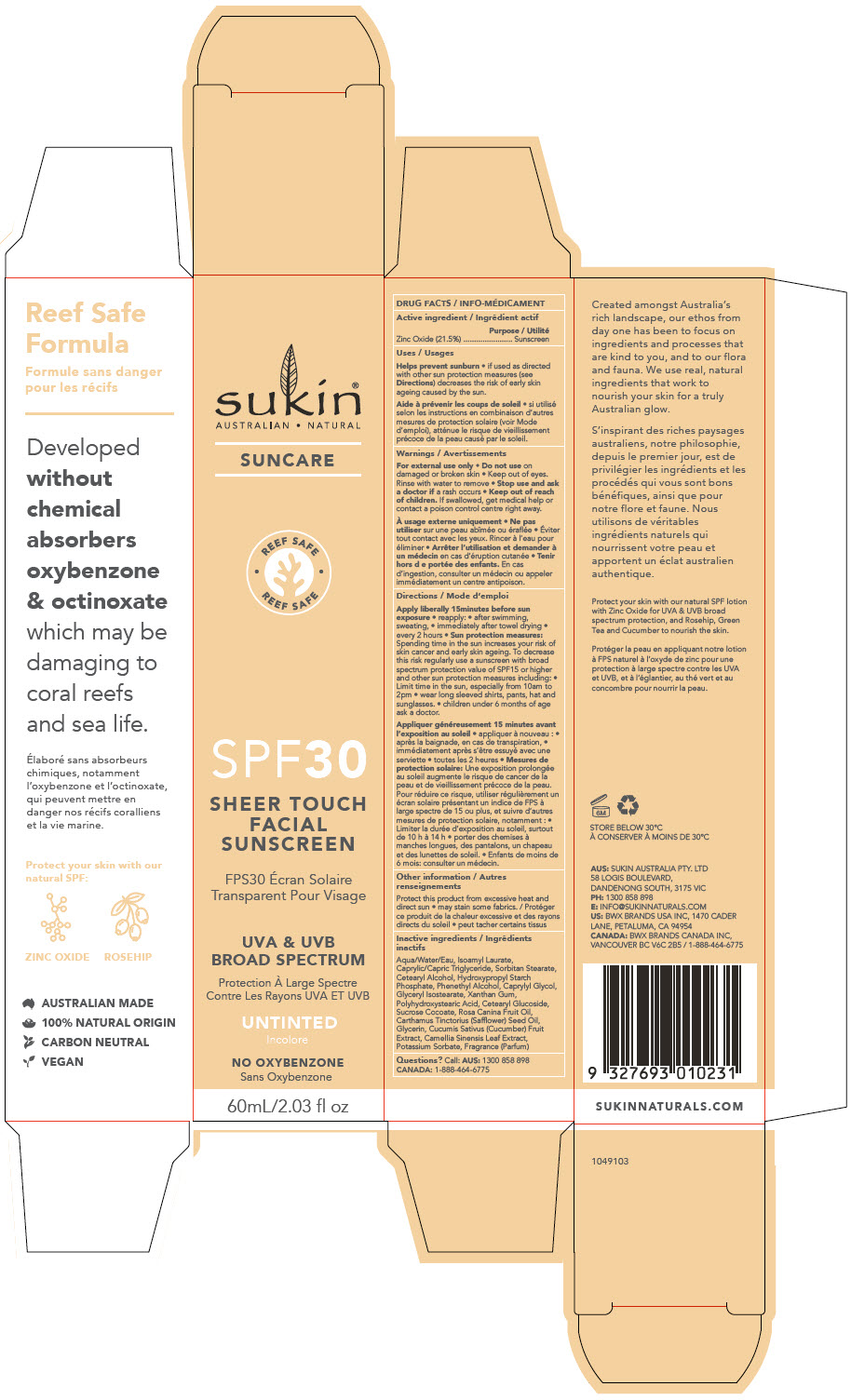 DRUG LABEL: SPF30 SHEER TOUCH FACIAL SUNSCREEN
NDC: 55560-5001 | Form: LOTION
Manufacturer: Andalou naturals
Category: otc | Type: HUMAN OTC DRUG LABEL
Date: 20201012

ACTIVE INGREDIENTS: ZINC OXIDE 215 mg/1 mL
INACTIVE INGREDIENTS: WATER; ISOAMYL LAURATE; MEDIUM-CHAIN TRIGLYCERIDES; SORBITAN MONOSTEARATE; CETOSTEARYL ALCOHOL; PHENYLETHYL ALCOHOL; CAPRYLYL GLYCOL; GLYCERYL ISOSTEARATE; XANTHAN GUM; CETEARYL GLUCOSIDE; SUCROSE COCOATE; ROSA CANINA FRUIT OIL; SAFFLOWER OIL; GLYCERIN; CUCUMBER; GREEN TEA LEAF; POTASSIUM SORBATE

SPF30 SHEER TOUCH FACIAL SUNSCREEN

DRUG FACTS

Active ingredient

Zinc Oxide (21.5%)

Purpose

Sunscreen

Uses

Helps prevent sunburn

- if used as directed with other sun protection measures (see Directions) decreases the risk of early skin ageing caused by the sun.

Warnings

For external use only

- Do not use on damaged or broken skin
- Keep out of eyes. Rinse with water to remove

- Stop use and ask a doctor if a rash occurs

- Keep out of reach of children. If swallowed, get medical help or contact a poison control centre right away.

Directions

Apply liberally 15minutes before sun exposure

- reapply:
  - after swimming, sweating,
  - immediately after towel drying
  - every 2 hours
- Sun protection measures: Spending time in the sun increases your risk of skin cancer and early skin ageing. To decrease this risk regularly use a sunscreen with broad spectrum protection value of SPF15 or higher and other sun protection measures including:
  - Limit time in the sun, especially from 10am to 2pm
  - wear long sleeved shirts, pants, hat and sunglasses.
  - children under 6 months of age ask a doctor.

Other information

Protect this product from excessive heat and direct sun

- may stain some fabrics.

Inactive ingredients

Aqua/Water/Eau, Isoamyl Laurate, Caprylic/Capric Triglyceride, Sorbitan Stearate, Cetearyl Alcohol, Hydroxypropyl Starch Phosphate, Phenethyl Alcohol, Caprylyl Glycol, Glyceryl Isostearate, Xanthan Gum, Polyhydroxystearic Acid, Cetearyl Glucoside, Sucrose Cocoate, Rosa Canina Fruit Oil, Carthamus Tinctorius (Safflower) Seed Oil, Glycerin, Cucumis Sativus (Cucumber) Fruit Extract, Camellia Sinensis Leaf Extract, Potassium Sorbate, Fragrance (Parfum)

Questions?

Call: AUS: 1300 858 898 CANADA: 1-888-464-6775

PRINCIPAL DISPLAY PANEL - 60 mL Tube Carton

sukin®
AUSTRALIAN • NATURAL

SUNCARE

• REEF SAFE •
REEF SAFE

SPF30

SHEER TOUCH
FACIAL
SUNSCREEN

UVA & UVB
BROAD SPECTRUM

UNTINTED

NO OXYBENZONE

60mL/2.03 fl oz